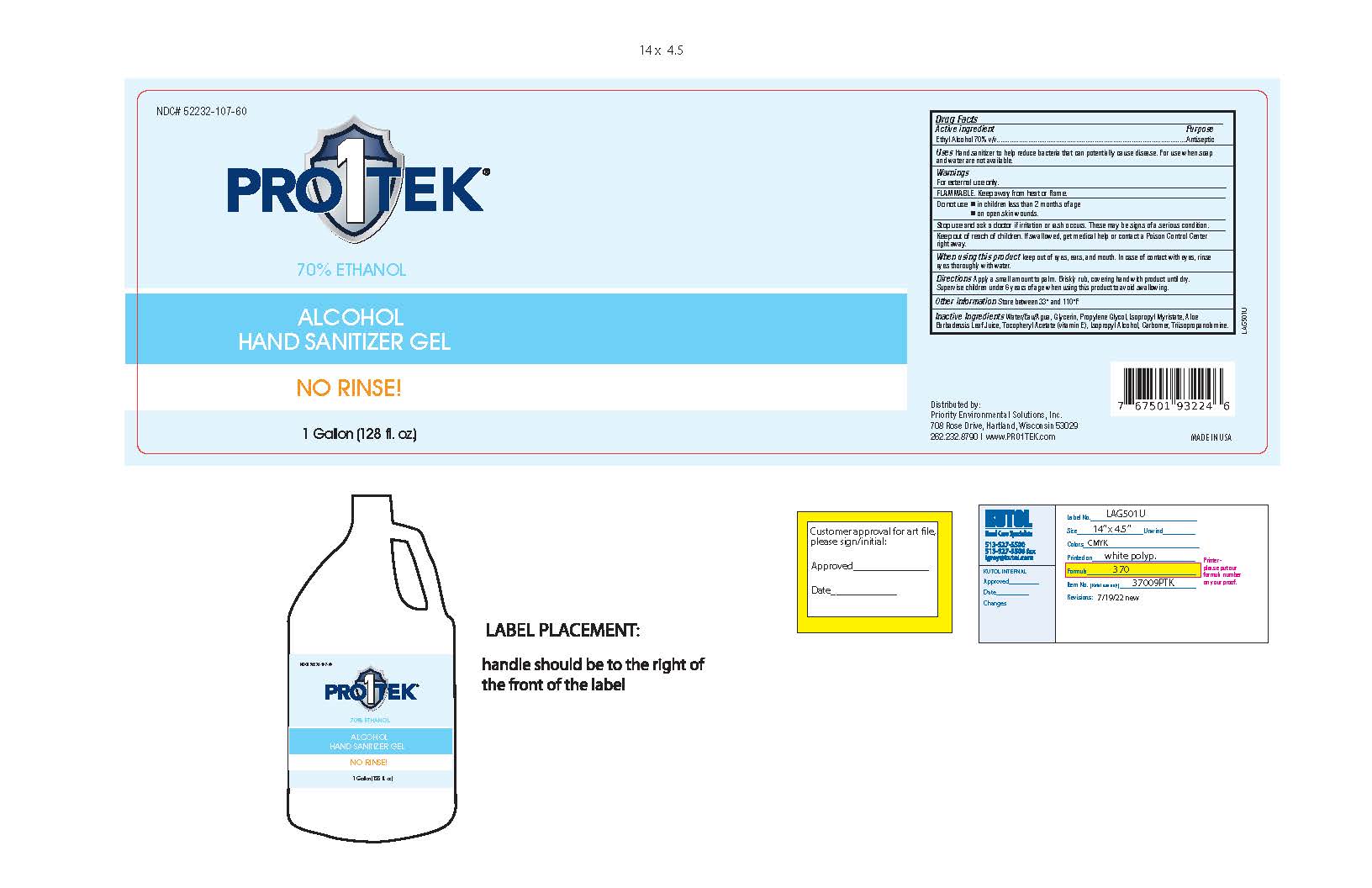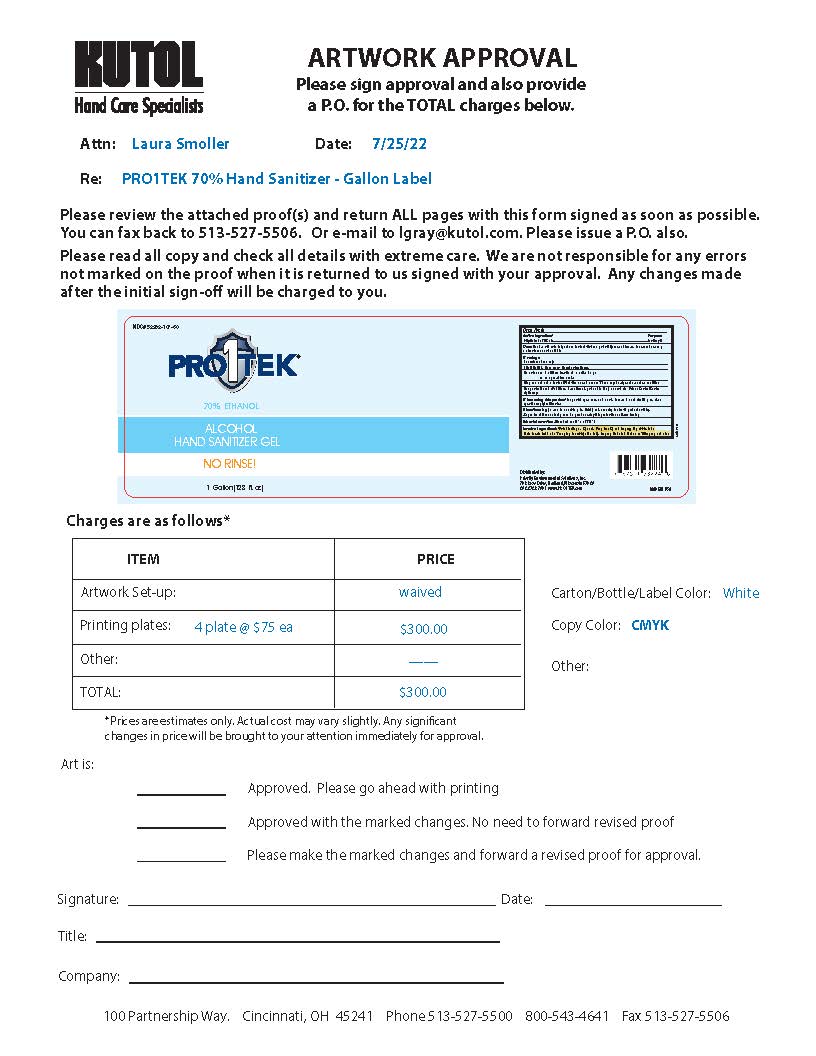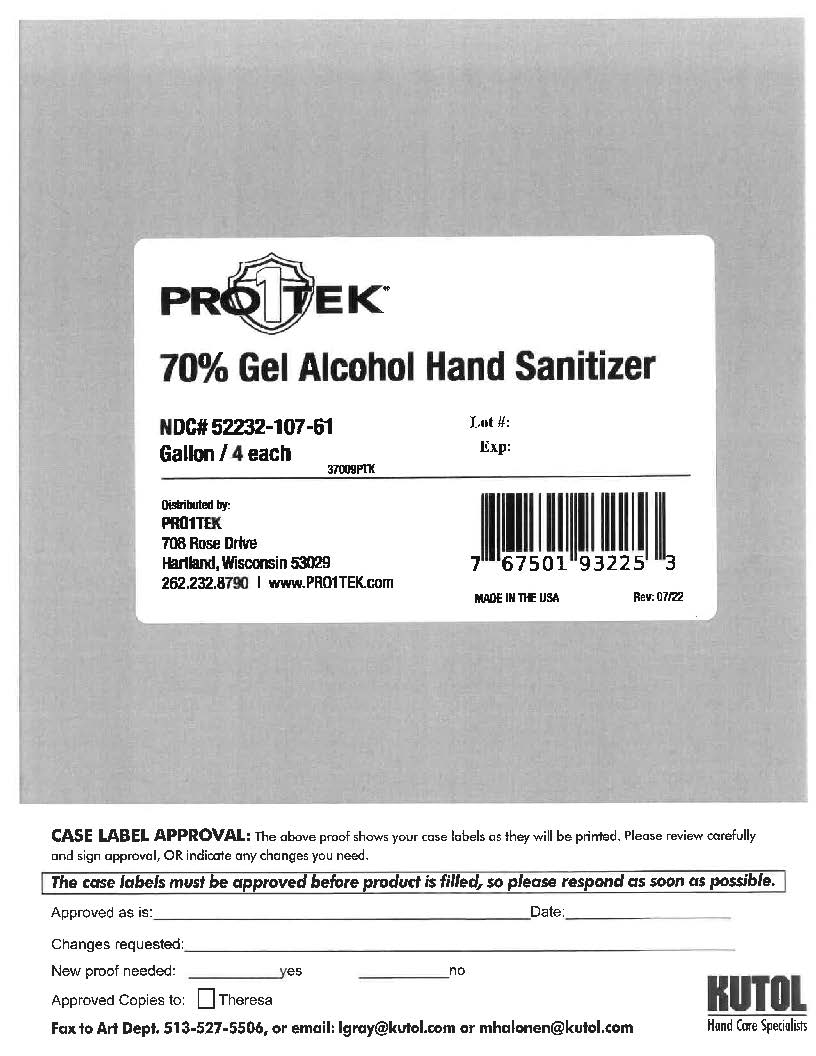 DRUG LABEL: Pro1tek Hand Sanitizer Gel
NDC: 52232-107 | Form: LIQUID
Manufacturer: Priority Environmental Solutions Inc.
Category: otc | Type: HUMAN OTC DRUG LABEL
Date: 20220809

ACTIVE INGREDIENTS: ALCOHOL 2650 mL/3785 mL
INACTIVE INGREDIENTS: ALOE VERA LEAF; ALPHA-TOCOPHEROL ACETATE; TRIISOPROPANOLAMINE; ISOPROPYL MYRISTATE; ISOPROPYL ALCOHOL; CARBOMER 940; WATER; GLYCERIN; POLYETHYLENE GLYCOL 600

Pro1tek Hand Sanitizer Gel

Active Ingredient

Ethyl Alcohol 70%

Purpose

Antiseptic

Uses

Hand Sanitizer to help reduce bacteria that potentially can cause disease. For use when soap and water are not available.

Warnings

For External Use Only. FLAMMABLE. Keep away from heat or flame.

Do not use

In children less than 2 months of age. On open skin wounds.

Stop use and ask a doctor.

If irritation or rash occurs. These may be signs of a serious condition.

Keep out of reach of children.

If swallowed, get medical help or contact a Poison Control Center right away.

When using this product

Keep out of eyes, ears, and mouth. In case of contact with eyes, rinse eyes thoroughly with water.

Directions

Apply a small amount to palm. Bristly rub, covering hand with product until dry. Supervise children under 6 years of age when using this product to avoid swallowing.

Other Information

Store between 33 and 110 F.

Inactive Ingredients

Water/Eau/Agua, Glycerin, Polyethylene glycol, Isopropyl Myristate, Aloe Barbadensis Leaf Juice, Tocopheryl Acetate (vitamin E), Isopropyl Alcohol, Carbomer, Triisopropanolamine